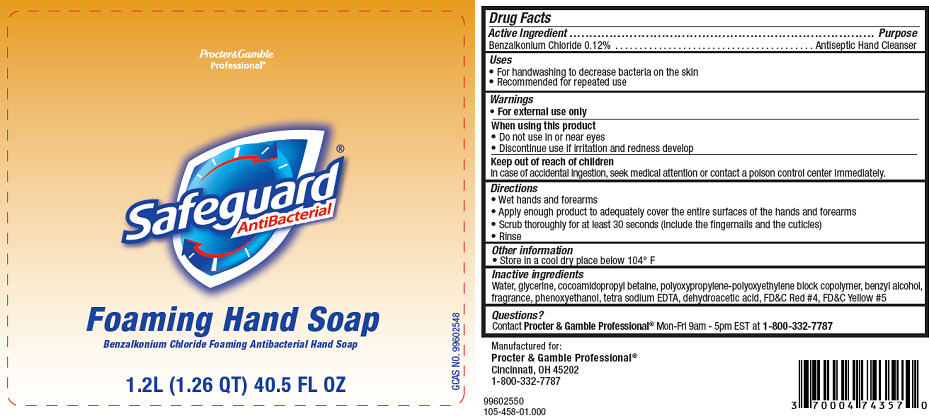 DRUG LABEL: Safeguard
NDC: 37000-601 | Form: SOAP
Manufacturer: The Procter & Gamble Manufacturing Company
Category: otc | Type: HUMAN OTC DRUG LABEL
Date: 20251218

ACTIVE INGREDIENTS: BENZALKONIUM CHLORIDE 0.12 g/100 mL
INACTIVE INGREDIENTS: GLYCERIN; COCAMIDOPROPYL BETAINE; BENZYL ALCOHOL; PHENOXYETHANOL; EDETATE SODIUM; WATER; DEHYDROACETIC ACID; FD&C RED NO. 4; FD&C YELLOW NO. 5

Safeguard® AntiBacterial Foaming Hand Soap

Drug Facts

Active Ingredient

Benzalkonium Chloride 0.12%

Purpose

Antiseptic Hand Cleanser

Uses

- For handwashing to decrease bacteria on the skin
- Recommended for repeated use

Warnings

- For external use only

When using this product

- Do not use in or near eyes

- Discontinue use if irritation and redness develop

Keep out of reach of children

In case of accidental ingestion, seek medical attention or contact a poison control center immediately.

Directions

- Wet hands and forearms
- Apply enough product to adequately cover the entire surfaces of the hands and forearms
- Scrub thoroughly for at least 30 seconds (include the fingernails and the cuticles)
- Rinse

Other information

- Store in a cool dry place below 104° F

Inactive ingredients

Water, glycerine, cocoamidopropyl betaine, polyoxypropylene-polyoxyethylene block copolymer, benzyl alcohol, fragrance, phenoxyethanol, tetra sodium EDTA, dehydroacetic acid, FD&C Red #4, FD&C Yellow #5

Questions?

Contact Procter & Gamble Professional® Mon-Fri 9am - 5pm EST at 1-800-332-7787

PRINCIPAL DISPLAY PANEL - 1.2 L Bag Label

Procter & Gamble
Professional®

Safeguard®
AntiBacterial

Foaming Hand Soap
Benzalkonium Chloride Foaming Antibacterial Hand Soap

1.2L (1.26 QT) 40.5 FL OZ